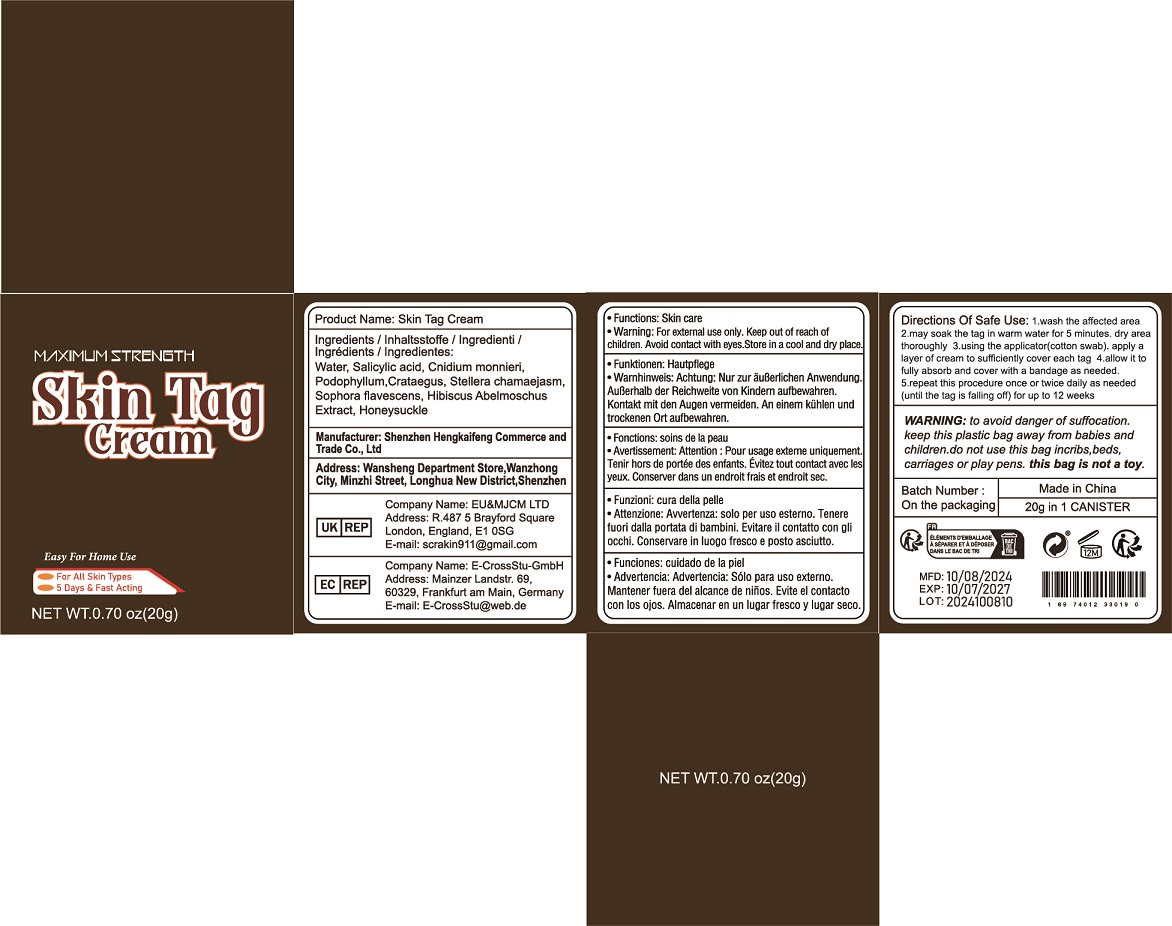 DRUG LABEL: Skin Tag Cream
NDC: 84117-035 | Form: CREAM
Manufacturer: Shenzhen Hengkaifeng Commerce and Trade Co., Ltd
Category: otc | Type: HUMAN OTC DRUG LABEL
Date: 20241018

ACTIVE INGREDIENTS: SALICYLIC ACID 10 mg/1 g
INACTIVE INGREDIENTS: WATER

ACTIVE INGREDIENT

Salicylic acid

Purpose

Skin Tag Cream

Use

Skin Tag Cream

Warnings

For adult external use only. Flammable.
Keep away from heat or flame
Do not use
* Pregnant women and children.
* on open skin wounds

Keep Out Of Reach Of Children

Directions Of Safe Use:

* 1-2 times per day.

Other information

Store between15-30C(59-86F)
Avoid freezing and excessive heat above
40C (104F)

Inactive ingredients

Water, Cnidium monnieri.Podophyllum,Crataegus, Stellera chamaejasm.Sophora flavescens, Hibiscus AbelmoschusExtract, Honeysuckle

DOSAGE & ADMINISTRATION

Take an appropriate amount of this product and apply it on the wart area